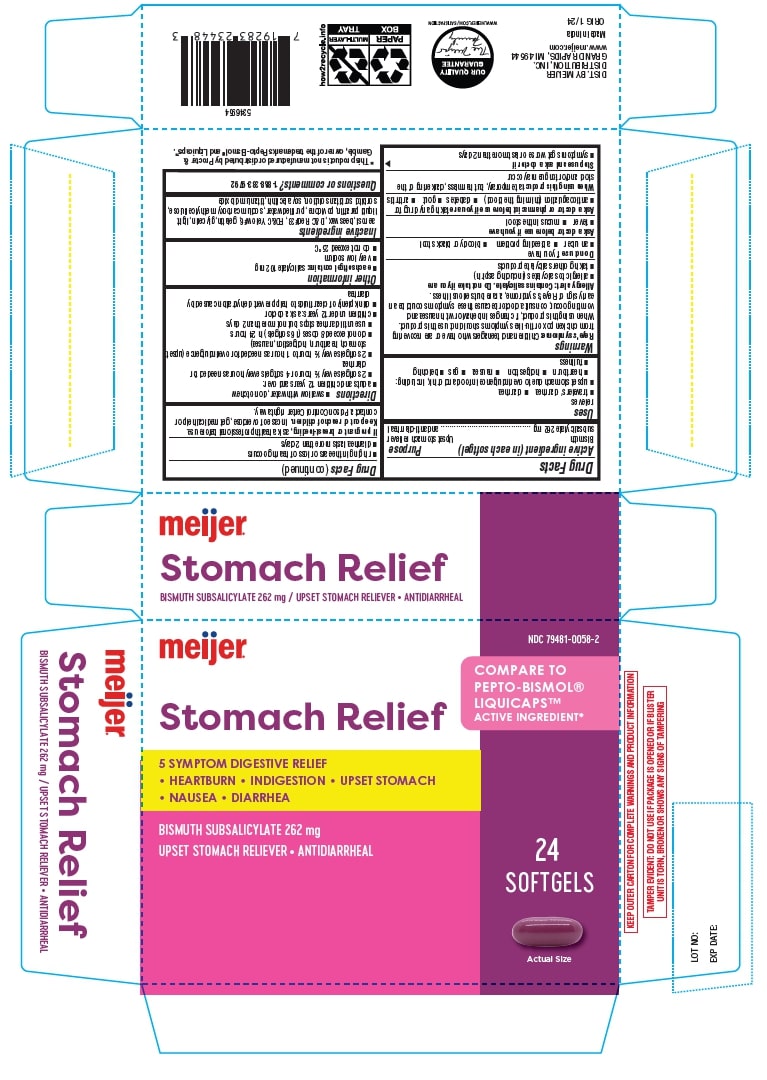 DRUG LABEL: Bismuth Subsalicylate
NDC: 79481-0058 | Form: CAPSULE, LIQUID FILLED
Manufacturer: Meijer, Inc.
Category: otc | Type: HUMAN OTC DRUG LABEL
Date: 20241220

ACTIVE INGREDIENTS: BISMUTH SUBSALICYLATE 262 mg/1 1
INACTIVE INGREDIENTS: SYNTHETIC BEESWAX; SILICON DIOXIDE; D&C RED NO. 33; FD&C YELLOW NO. 6; GELATIN; GLYCERIN; PARAFFIN; POVIDONE; WATER; CARBOXYMETHYLCELLULOSE SODIUM; SORBITOL SOLUTION; LECITHIN, SOYBEAN; TITANIUM DIOXIDE

Stomach Relief

Drug Facts

Ask a doctor before use if you have
• fever • mucus in the stool